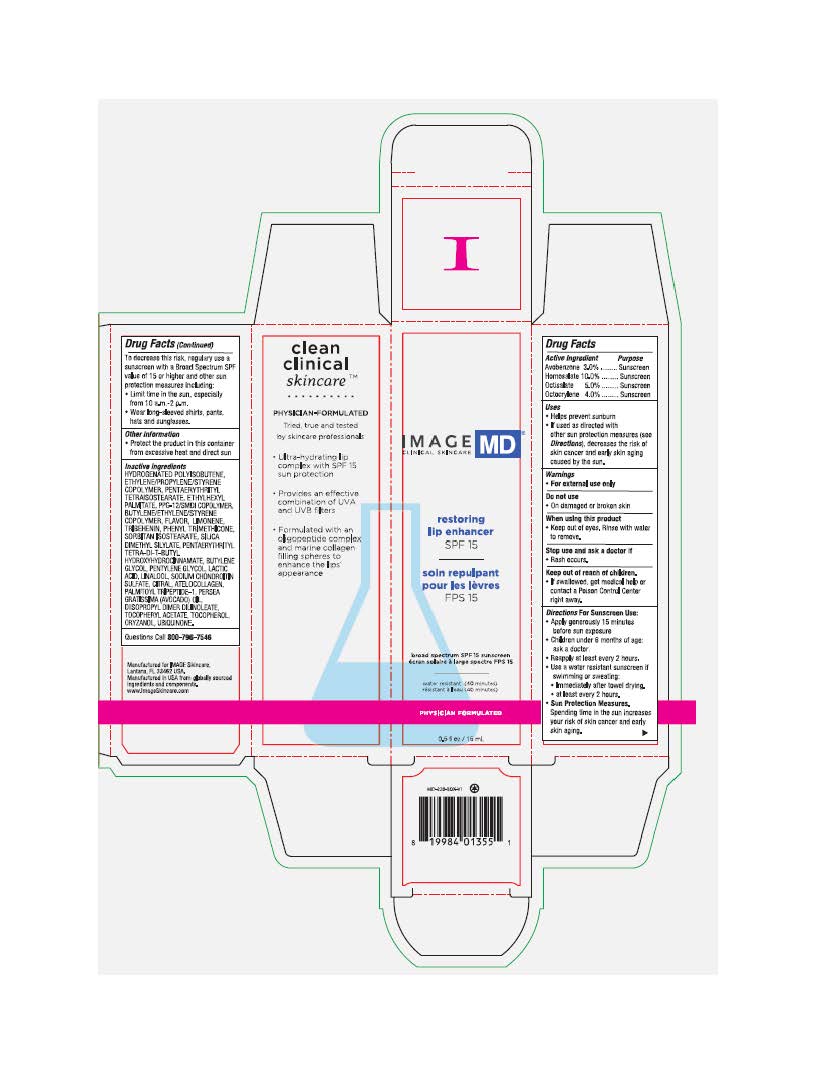 DRUG LABEL: Image MD Restoring Lip Enhancer SPF15
NDC: 60232-3537 | Form: CREAM
Manufacturer: Swiss-American CDMO, LLC
Category: otc | Type: HUMAN OTC DRUG LABEL
Date: 20231106

ACTIVE INGREDIENTS: OCTISALATE 50 g/1000 g; AVOBENZONE 30 g/1000 g; HOMOSALATE 100 g/1000 g; OCTOCRYLENE 40 g/1000 g
INACTIVE INGREDIENTS: PENTAERYTHRITYL TETRAISOSTEARATE; PPG-12/SMDI COPOLYMER; ETHYLHEXYL PALMITATE; LIMONENE, (+)-; TRIBEHENIN; PHENYL TRIMETHICONE; SORBITAN ISOSTEARATE; SILICA DIMETHYL SILYLATE; BUTYLENE GLYCOL; PENTYLENE GLYCOL; LACTIC ACID; LINALOOL, (+)-; SODIUM CHONDROITIN SULFATE (PORCINE; 5500 MW); CITRAL; PALMITOYL TRIPEPTIDE-1; AVOCADO OIL; .ALPHA.-TOCOPHEROL ACETATE; TOCOPHEROL; HYDROGENATED POLYBUTENE (1300 MW); PENTAERYTHRITOL TETRAKIS(3-(3,5-DI-TERT-BUTYL-4-HYDROXYPHENYL)PROPIONATE); DIISOPROPYL DILINOLEATE; ORYZANOL; UBIDECARENONE

Image MD Restoring Lip Enhancer SPF15

Warnings

For external use only. Do not use on damaged or broken skin. When using this product keep out of eyes. Rinse with water to remove. Stop use and ask doctor if rash occurs. If swallowed get medical help or contact a Poison Control Center right away.

Active Ingredients

Avobenzone 3.0% Sunscreen

Homosalate 10.0% Sunscreen

Octisalate 5.0% Sunscreen

Octocrylene 4.0% Sunscreen

Indications & Usage

Helps prevent sunburn. If used as directed with other sun protection measure (See Directions), decreases the risk of skin cancer and early skin aging caused by the sun.

Keep out of reach of children

Directions

Apply liberally 15 minutes before sun exposure. Use a water-resistant sunscreen if swimming or sweating. Reapply at least every 2 hours. Sun Protection Measures: Spending time in the sun increases your risk of skin cancer and early skin aging. To decrease this risk, regularly use a sunscreen with a broad-spectrum SPF of 15 or higher and other sun protection measures including: limit time in the sun, especially from 10 am to 2 pm. Wear long-sleeve shirts, pants, hats, and sunglasses. Children under 6 months: ask a physician.

Directions

Apply liberally 15 minutes before sun exposure. Use a water-resistant sunscreen if swimming or sweating. Reapply at least every 2 hours. Sun Protection Measures: Spending time in the sun increases your risk of skin cancer and early skin aging. To decrease this risk, regularly use a sunscreen with a broad-spectrum SPF of 15 or higher and other sun protection measures including: limit time in the sun, especially from 10 am to 2 pm. Wear long-sleeve shirts, pants, hats, and sunglasses. Children under 6 months: ask a physician.

Other information

Protect the product in this container from excessive heat and direct sun.

Inactive ingredients

hydrogenated polyisobutene, ethylene/propylene/styrene copolymer, Pentaerythrityl Tetraisostearate, ethylhexyl palmitate, PPG-12/SMDI Copolymer, butylene/ethylene/styrene copolymer, flavor, limonene, tribehenin, phenyl trimethicone, sorbitan isostearate, silican dimethyl silylate, Pentaerythrityl Tetra-di-t-butyl Hydroxyhydrocinnamate, butylene glycol, pentylene glycol, lactic acid, linalool, sodium chondrotin sulfate, citral, atelocollagen, palmitoyl tripeptide-1, Avacodo (Persea gratissima) Oil, Diisopropyl Dimer Dilinoleate, Tocopheryl Acetate, Tocopherol, Oryzanol, Ubiquinone.

Questions

Questions call 800-796-7546